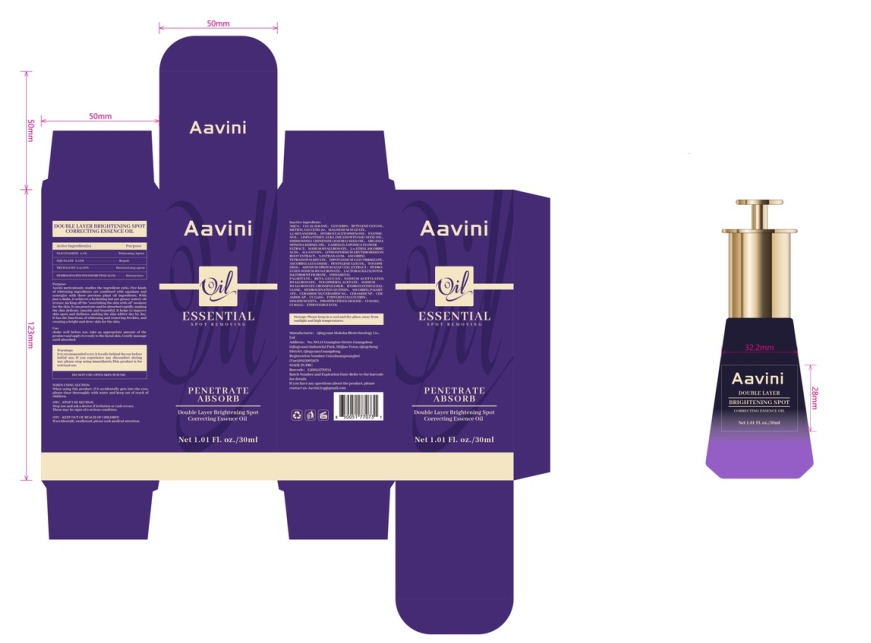 DRUG LABEL: Aavini Double Layer Brightening Spot Correcting Essence Oil
NDC: 85004-001 | Form: LIQUID
Manufacturer: Qingyuan Moksha Biotechnology Co., Ltd.
Category: otc | Type: HUMAN OTC DRUG LABEL
Date: 20250310

ACTIVE INGREDIENTS: SQUALANE 0.15 g/100 mL; TREHALOSE 0.4116 g/100 mL; HYDROGENATED POLYBUTENE (1300 MW) 25.8 g/100 mL; NIACINAMIDE 2.1 g/100 mL
INACTIVE INGREDIENTS: LITHOSPERMUM ERYTHRORHIZON ROOT; ALLANTOIN; TOCOPHEROL; CERAMIDE AP; ETHYLHEXYL PALMITATE; CI 61565; ALPHA-TOCOPHEROL ACETATE; PEG-9 DIGLYCIDYL ETHER/SODIUM HYALURONATE CROSSPOLYMER; CI 60725; LIMNANTHES ALBA (MEADOWFOAM) SEED OIL; EDETATE DISODIUM; CERAMIDE NS; ASCORBYL TETRAISOPALMITATE; ETHYLHEXYLGLYCERIN; ETHOXYDIGLYCOL; SODIUM HYALURONATE; SODIUM BUTYROYL/FORMOYL HYALURONATE; 1,2-HEXANEDIOL; PANTHENOL; SIMMONDSIA CHINENSIS (JOJOBA) SEED OIL; ARGANIA SPINOSA KERNEL OIL; 3-O-ETHYL ASCORBIC ACID; DIPOTASSIUM GLYCYRRHIZATE; ASCORBYL PALMITATE; CERAMIDE NP; CI 73360; PENTYLENE GLYCOL; AQUA; C15-19 ALKANE; GLYCERIN; BUTYLENE GLYCOL; METHYL GLUCETH-20; MAGNESIUM SULFATE; SODIUM ACETYLATED HYALURONATE; HYDROXYETHYLCELLULOSE; HYDROGENATED SOYBEAN LECITHIN; HYDROXYACETOPHENONE; CAMELLIA JAPONICA FLOWER; XANTHAN GUM; SODIUM CARBOXYMETHYL .BETA.-GLUCAN (DS 0.65-0.85); PHOSPHATIDYLCHOLINE, SOYBEAN; LACTOBACILLUS; ADENIUM OBESUM LEAF; ASCORBYL GLUCOSIDE

85004-001

Active Ingredient(s)

NIACINAMIDE 2.1%
SQUALANE 0.15%
TREHALOSE 0.4116%
HYDROGENATED POLYISOBUTENE 25.8%

Purpose

Whitening Agent
Repair
Moisturizing agent
Moisturizer

Use

shake well before use, take an appropriate amount of the
product and apply it evenly to the facial skin. Gently massage
until absorbed.

Warnings

It is recommended to try it locally behind the ear before initial use; If you experience any discomfort during
use, please stop using immediately.This product is for external use.

Do not use

OPEN SKIN WOUND

When using this product, if it accidentally gets into the eyes, please rinse thoroughly with water and keep out of reach of
children.

Stop use and ask a doctor if irritation or rash occurs. These may be signs of a serious condition.

KEEP OUT OF REACH OF CHILDREN

If accidentally swallowed, please seek medical attention.

Directions

Apply proper amount of whitening and spot lightening essence evenly on the face, which can be gently massaged to help absorb

Other information

Please keep in a cool and dry place, away from sunlight and high temperatures.

Inactive ingredients

AQUA、C15-19 ALKANE、GLYCERIN BUTYLENE GLYCOL METHYL GLUCETH-20、MAGNESIUM SULFATE、
1,2- HEXANEDIOL、HYDROXYACETOPHENONE PANTHE-NOL、LIMNANTHES ALBA (MEADOWFOAM) SEED OIL、
SIMMONDSIA CHINENSIS (JOJOBA) SEED OIL、ARGANIA SPINOSA KERNEL OIL、CAMELLIA JAPONICA FLOWER
EXTRACT、SODIUM HYALURONATE、3-0- ETHYL ASCORBIC ACID、ALLANTOIN LITHOSPERMUM ERYTHRORHIZON
ROOT EXTRACT、XANTHAN GUM、ASCORBYL TETRAISOPALMITATE、DIPOTASSIUM GLYCYRRHIZATE、
ASCORBYL GLUCOSIDE、PENTYLENE GLYCOL、TOCOPH-EROL、ADENIUM OBESUM LEAF CELL EXTRACT、HYDRO-
LYZED SODIUM HYALURONATE、LACTOBACILLUS/SOYM-ILK FERMENT FILTRATE、ETHYLHEXYL
PALMITATE、BETA-GLUCAN、 SODIUM ACETYLATED HYALURONATE、TOCOPHERYL ACETATE、SODIUM
HYALURONATE CROSSPOLYMER、HYDROXYETHYLCELL-ULOSE、HYDROGENATED LECTTHIN、

ASCORBYL PALMIT-ATE CERAMIDE NS/CERAMIDE NG、CERAMIDENP、 CER-AMIDE AP、CI 73360、ETHYLHEXYLGLYCERIN、DISODIUM EDTA、PHOSPHATIDYLCHOLINE、 CI 61565、CI 60725、ETHOXYDIGLYCOL